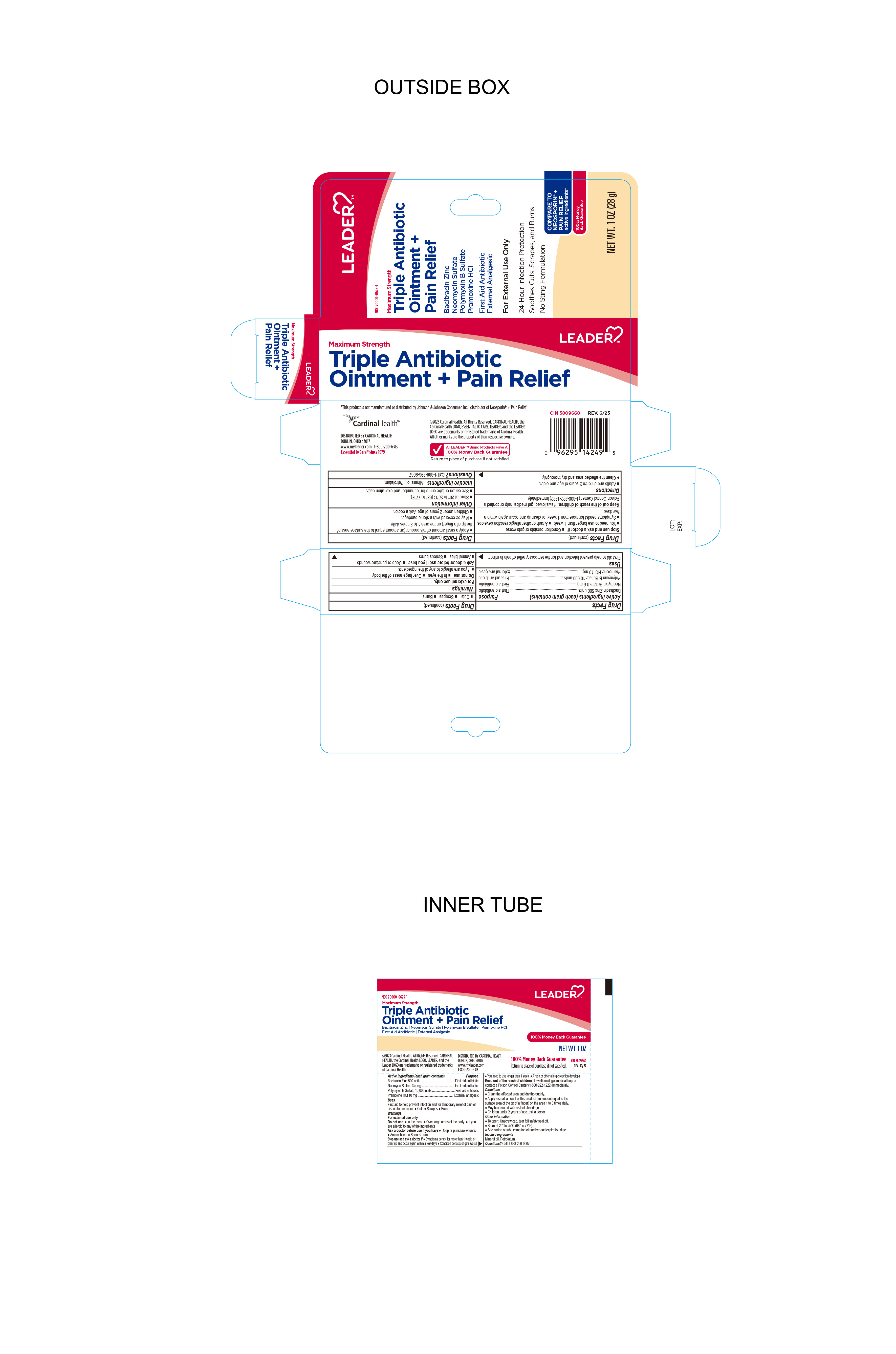 DRUG LABEL: Leader Triple antibiotic and pain relief
NDC: 70000-0625 | Form: OINTMENT
Manufacturer: Cardinal Health 110 dba LEADER
Category: otc | Type: HUMAN OTC DRUG LABEL
Date: 20250513

ACTIVE INGREDIENTS: BACITRACIN ZINC 500 [USP'U]/1 g; NEOMYCIN SULFATE 3.5 mg/1 g; PRAMOXINE HYDROCHLORIDE 10 mg/1 g; POLYMYXIN B SULFATE 10000 [USP'U]/1 g
INACTIVE INGREDIENTS: PETROLATUM; LIGHT MINERAL OIL

Leader Triple Antibiotic Ointment + Pain Relief

Active Ingredient

Bacitracin zinc 500 Units

Purpose

First Aid Antibiotic

Active Ingredient

Neomycin Sulfate 3.5mg

Purpose

First Aid Antibiotic

Active Ingredient

Polymyxin B Sulfate 10,000 Units

Purpose

First Aid Antibiotic

Active Ingredient

Pramoxine HCL 10mg

Purpose

External Analgesic

Uses

First Aid to help prevent infection and for temporary relief of pain or discomfort in minor

- Cuts
- Scrapes
- Burns

Warnings

For external use only. Do not use:

- In eyes
- Over large areas of the body
- If you are allergic to any of the ingredients

Ask a Doctor before Use

Ask Doctor before use if you have:

- Deep or puncture wouns
- Animal bites
- Serious burns

Stop Use and ask a Doctor if:

- Symptoms persists for more than 1 week or clear up and occur again within a few days.
- Condition persists or gets worse
- You need to use longer than 1 week
- A rash or other allergic reaction develops

Keep out of Reach of Children

If Swallowed, get medical help or contact a Poison Control Center (1-800-222-1222) immediately.

Directions

Adults and children 2 years of age and older.

- Clean the affected area and dry thoroughly
- Apply a small amount of this product (an amount equal to the surface area of the tip of a finger) on the area 1 to 3 times daily
- May be covered with a sterile bandage
- Children under 2 years of age: ask doctor

Other Information

- Store at 20° to 25°C (68° to 77°F)
- See carton or tube crimp for lot number and expiration date

Inactive Ingredient:

mineral oil, Petrolatum

Questions?

Call 1-888-296-9067

Distributed By:

Cardinal Health

Dublin, Ohio 43017

www.myleader.com

1-800-200-6313

Essential to care since 1979

This product is not manufactured or distributed by Johnson & Johnson a registered trademark of Neosporin Plus Pain Relief

©Cardinal Health. All rights reserved, CARDINAL HEALTH the Cardinal health LOGO, ESSENTIAL TO CARE, LEADER, and the LEADER LOGO are trademarks or registered trademarks of Cardinal Health. All other marks are the property of their respective owners.